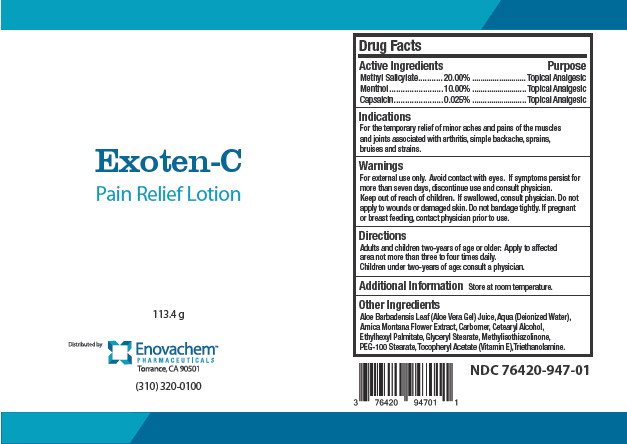 DRUG LABEL: EXOTEN-C
NDC: 76420-947 | Form: LOTION
Manufacturer: Asclemed USA, Inc.
Category: otc | Type: HUMAN OTC DRUG LABEL
Date: 20231016

ACTIVE INGREDIENTS: METHYL SALICYLATE 20 g/100 g; MENTHOL 10 g/100 g; CAPSAICIN 0.025 g/100 g
INACTIVE INGREDIENTS: ALOE VERA LEAF; WATER; ARNICA MONTANA FLOWER; CETOSTEARYL ALCOHOL; ETHYLHEXYL PALMITATE; GLYCERYL STEARATE SE; METHYLISOTHIAZOLINONE; PEG-100 STEARATE; .ALPHA.-TOCOPHEROL

Drug Facts

Active Ingredients

Methyl Salicylate 20.000%

Menthol 10.00%

Capsaicin 0.025%

Purpose

Topical Analgesic

Topical Analgesic

Topical Analgesic

Indications

For the temporary relief of minor aches and pains of the muscles and joints associated with arthritis, simple backache, sprains, bruises and strains.

Warnings

For external use only. Avoid contact with eyes.

ASK DOCTOR

If symptoms persist for more than seven days, discontinue use and consult physician.

Keep out of reach of children. If swallowed, consult physician.

DO NOT USE

Do not apply to wounds or damaged skin. Do not bandage tightly.

PREGNANCY OR BREAST FEEDING

If pregnant or breast feeding, contact physician prior to use.

Directions

Adults and children two-years of age or older: Apply to affected area not more than three to four times daily.

Children under two-years of age consult a physician.

Additional Information

Store at room temperature.

Other Ingredients

Aloe Barbadensis Leaf (Aloe Vera Gel) Juice; Aqua (Deionized Water); Arnica Montana Flower Extract; Carbomer, Cetearyl Alcohol, Ethylexyl Palmitate, Glyceryl Stearate, Methylisothiazolinone, PEG-100 Stearate, Tocopheryl Acetate (Vitamin E), Triethanolamine.

Principal Display Panel - Exoten-C Label

Exoten-C

Pain Relief  Lotion

113.4 g

Distributed by Enovachem™

PHARMACEUTICALS

Torrance, CA 90501

(310) 320-0100